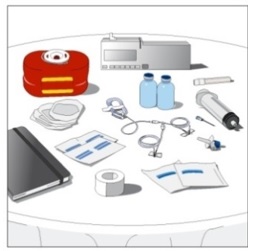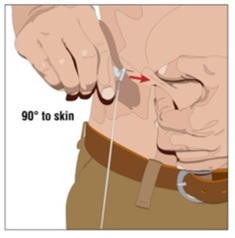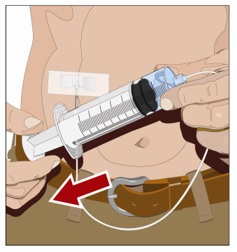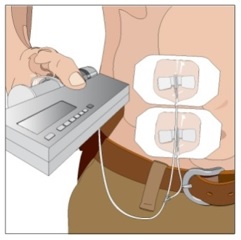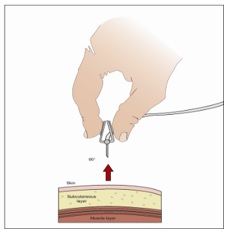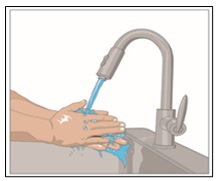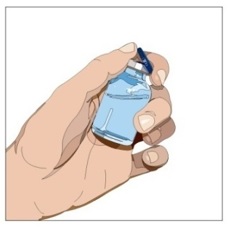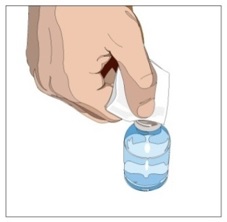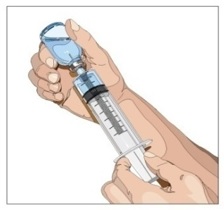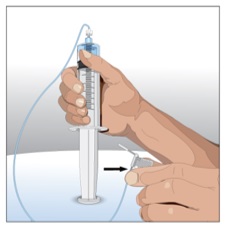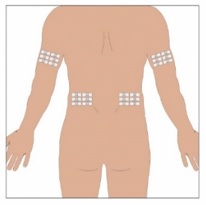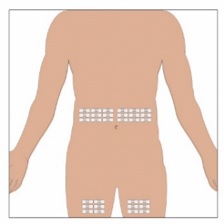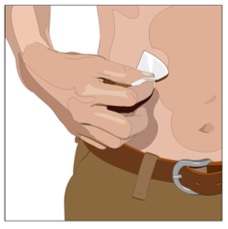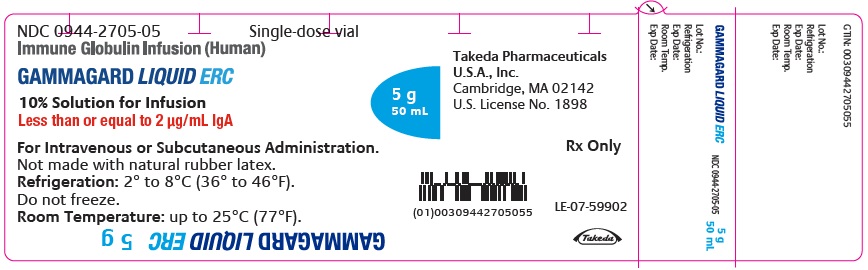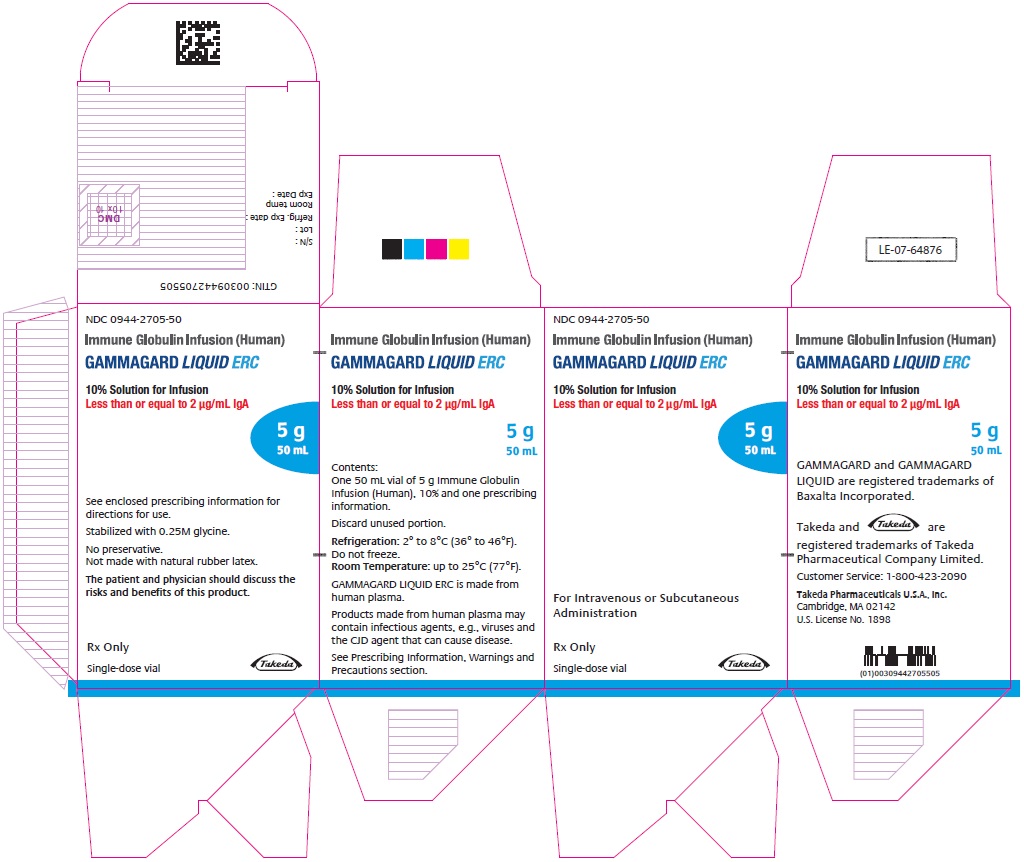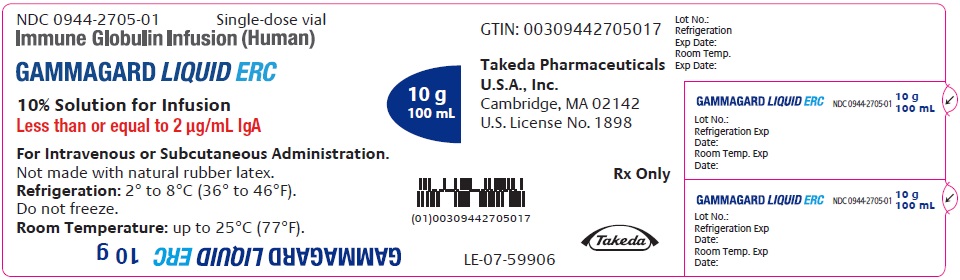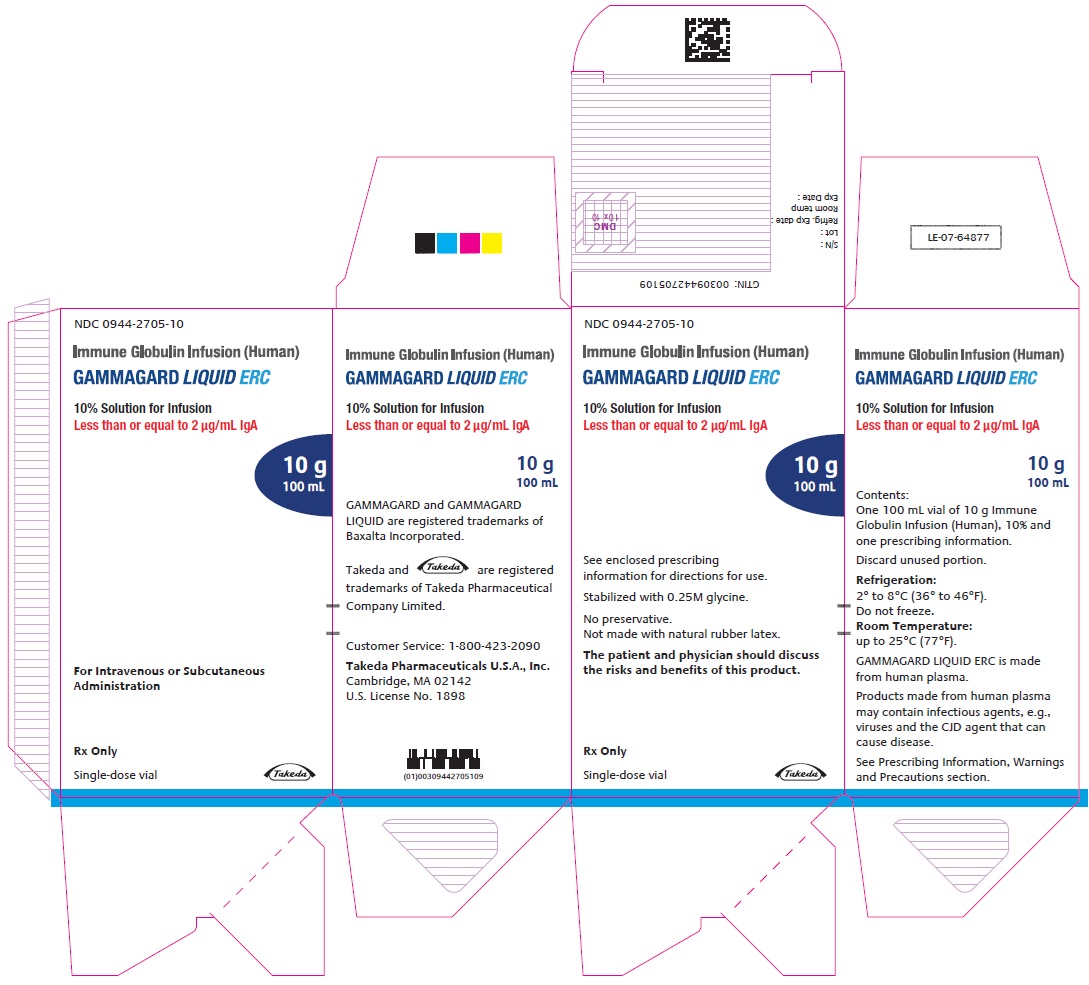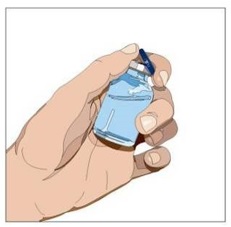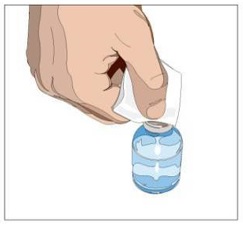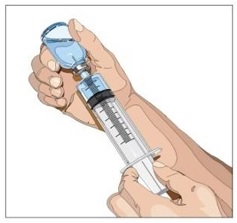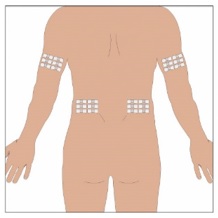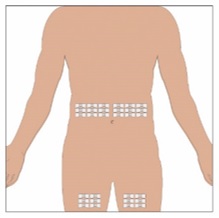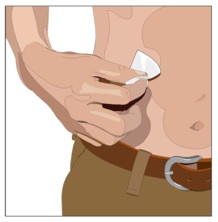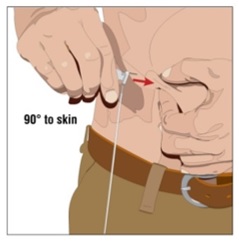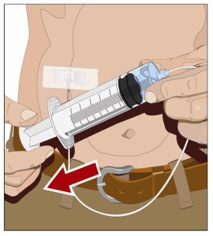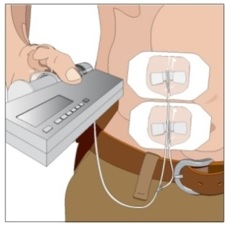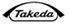 DRUG LABEL: GAMMAGARD Liquid ERC
NDC: 0944-2705 | Form: INJECTION, SOLUTION
Manufacturer: Takeda Pharmaceuticals America, Inc.
Category: other | Type: PLASMA DERIVATIVE
Date: 20251030

ACTIVE INGREDIENTS: HUMAN IMMUNOGLOBULIN G 100 mg/1 mL
INACTIVE INGREDIENTS: GLYCINE

HIGHLIGHTS OF PRESCRIBING INFORMATION

These highlights do not include all the information needed to use GAMMAGARD LIQUID® ERC safely and effectively. See full prescribing information for GAMMAGARD LIQUID ERC.
GAMMAGARD LIQUID ERC [immune globulin infusion (human)]
10% solution for intravenous, or subcutaneous use
Initial U.S. Approval: 2025

WARNING: THROMBOSIS, RENAL DYSFUNCTION and ACUTE RENAL FAILURE

See full prescribing information for complete boxed warning.

- Thrombosis may occur with immune globulin products, including GAMMAGARD LIQUID ERC. Risk factors include advanced age, prolonged immobilization, hypercoagulable conditions, history of venous or arterial thrombosis, use of estrogens, indwelling vascular catheters, hyperviscosity and cardiovascular risk factors. (5.4)
- Renal dysfunction, acute renal failure, osmotic nephrosis, and death may occur in predisposed patients with immune globulin intravenous (IGIV) products including GAMMAGARD LIQUID ERC. Renal dysfunction and acute failure occur more commonly with IGIV products containing sucrose. GAMMAGARD LIQUID ERC does not contain sucrose. (5.2)
- For patients at risk of thrombosis, administer GAMMAGARD LIQUID ERC at the minimum dose and infusion rate practicable. Ensure adequate hydration in patients before administration. Monitor for signs and symptoms of thrombosis and assess blood viscosity in patients at risk of hyperviscosity. (5.4)

1 INDICATIONS AND USAGE

GAMMAGARD LIQUID ERC is a replacement therapy for primary humoral immunodeficiency (PI) in adult and pediatric patients two years of age and older. (1)

2 DOSAGE AND ADMINISTRATION

Intravenous (IV) Administration: (2.1)

Dose | Initial Infusion Rate | Maintenance Infusion Rate
300 to 600 milligrams (mg)/kilograms (kg) every 3 to 4 weeks based on clinical response (2.1) | 0.5 milliliters (mL)/kg/hour (hr) (0.8 mg/kg/ minutes (min) for 30 minutes | Increase every 30 minutes (if tolerated) up to 5 mL/kg/hr (8 mg/kg/min)

Subcutaneous (SC) Administration: (2.1)

Dose | Initial Infusion Rate | Maintenance Infusion Rate
Initial dose: 1.37 × previous IV dose divided by # of weeks between IV doses. Maintenance dose: Based on clinical response and target immunoglobulin G (IgG) trough level. (2.1) | 40 kg body weight (BW) and greater: 30 mL/site at 20 mL/hr/site Under 40 kg BW: 20 mL/site at 15 mL/hr/site | 40 kg BW and greater: 30 mL/site at 20 to 30 mL/hr/site Under 40 kg BW: 20 mL/site at 15 to 20 mL/hr/site

3 DOSAGE FORMS AND STRENGTHS

- GAMMAGARD LIQUID ERC is available as an immune globulin (Human) 10% (100 mg/mL) solution with less than or equal to 2 micrograms (µg)/mL immunoglobulin A (IgA). (3)
- GAMMAGARD LIQUID ERC is available in a 50 mL and 100 mL single-dose vial. (3)

4 CONTRAINDICATIONS

- History of anaphylactic or severe systemic hypersensitivity reactions to the administration of GAMMAGARD LIQUID ERC. (4)

5 WARNINGS AND PRECAUTIONS

- Hypersensitivity Reactions: In case of a severe hypersensitivity reaction, discontinue GAMMAGARD LIQUID ERC infusion, and manage as appropriate. (5.1)
- Renal Injury: Ensure patients are not volume depleted before administering GAMMAGARD LIQUID ERC. Monitor renal function, including blood urea nitrogen, serum creatinine, and urine output in patients receiving GAMMAGARD LIQUID ERC prior to initial infusion and at appropriate intervals thereafter. (5.2)
- Hyperproteinemia, hyperviscosity, and hyponatremia may occur. (5.3)
- Thrombosis: Monitor for signs and symptoms of thrombosis. (5.4)
- Aseptic Meningitis Syndrome (AMS): Conduct neurological examination on patients exhibiting symptoms and signs of AMS. (5.5)
- Hemolysis: Monitor for clinical signs and symptoms of hemolysis. (5.6)
- Transfusion-Related Acute Lung Injury (TRALI): Monitor patients for symptoms of TRALI and manage using oxygen therapy with adequate ventilatory support as appropriate. (5.7)
- Transmission of infectious disease: GAMMAGARD LIQUID ERC is made from human blood, it may carry a risk of transmitting infectious agents. (5.8)

6 ADVERSE REACTIONS

The most common adverse reactions (incidence ≥5%) were: (6.1)

Intravenous Administration: Headache, fatigue, pyrexia, chills, nausea, pain in extremity, diarrhea, migraine, vomiting, dizziness, urticaria, cough, asthma, oropharyngeal pain, infusion site extravasation, arthralgia, rash, myalgia, pruritus, and cardiac murmur. (6.1)

Subcutaneous Administration: Infusion site (local) event, headache, pyrexia, fatigue, heart rate increased, abdominal pain upper, vomiting, arthralgia, nausea, asthma, blood pressure systolic increased, diarrhea, ear pain, aphthous ulcer, migraine, oropharyngeal pain, and pain in extremity. (6.1)

To report SUSPECTED ADVERSE REACTIONS, contact Takeda Pharmaceuticals U.S.A., Inc. at 1-877-TAKEDA-7 (1-877-825-3327) or FDA at 1-800-FDA-1088 or www.fda.gov/medwatch.

7 DRUG INTERACTIONS

Passive transfer of antibodies may transiently interfere with immune responses to live virus vaccines, such as measles, mumps, rubella, and varicella. (7)

8 USE IN SPECIFIC POPULATIONS

Geriatric: In patients over age 65 or in any patient at risk of developing renal insufficiency, do not exceed the recommended dose. Infuse GAMMAGARD LIQUID ERC at the minimum infusion rate practicable. (8.5)

FULL PRESCRIBING INFORMATION

WARNING: THROMBOSIS, RENAL DYSFUNCTION and ACUTE RENAL FAILURE

- Thrombosis may occur with immune globulin products, including GAMMAGARD LIQUID ERC. Risk factors may include advanced age, prolonged immobilization, hypercoagulable conditions, history of venous or arterial thrombosis, use of estrogens, indwelling vascular catheters, hyperviscosity and cardiovascular risk factors. Thrombosis may occur in the absence of known risk factors [see Warnings and Precautions (5.4)].
- Renal dysfunction, acute renal failure, osmotic nephrosis, and death may occur in predisposed patients with immune globulin intravenous (IGIV) products. Patients predisposed to renal dysfunction include those with any degree of pre-existing renal insufficiency, diabetes mellitus, age greater than 65, volume depletion, sepsis, paraproteinemia, or patients receiving known nephrotoxic drugs. Renal dysfunction and acute renal failure occur more commonly in patients receiving IGIV products containing sucrose. GAMMAGARD LIQUID ERC does not contain sucrose [see Warnings and Precautions (5.2)].
- For patients at risk of thrombosis, administer GAMMAGARD LIQUID ERC at the minimum dose and infusion rate practicable. Ensure adequate hydration in patients before administration. Monitor for signs and symptoms of thrombosis and assess blood viscosity in patients at risk of hyperviscosity [see Dosage and Administration (2.3), Warnings and Precautions (5.4)].

1 INDICATIONS AND USAGE

GAMMAGARD LIQUID ERC is indicated as replacement therapy for primary humoral immunodeficiency (PI) in adult and pediatric patients two years of age and older. This includes, but is not limited to, common variable immunodeficiency (CVID), X-linked agammaglobulinemia, congenital agammaglobulinemia, Wiskott-Aldrich syndrome, and severe combined immunodeficiencies.

2 DOSAGE AND ADMINISTRATION

2.1 Recommended Dosage

For intravenous (IV) or subcutaneous (SC) use only.

Intravenous Administration

Table 1: Recommended Dosage for Intravenous Administration
Dosage | Initial Infusion Rate | Maintenance Infusion Rate
300 to 600 milligrams (mg)/kilograms (kg) every 3 to 4 weeks | 0.5 milliliters (mL)/kg/hour (hr) (0.8 mg/kg/minutes (min) for 30 minutes | Increase every 30 minutes (if tolerated) up to 5 mL/kg/hr (8 mg/kg/min)

- Adjust frequency and dosage to achieve target serum immunoglobulin G (IgG) levels and clinical response.
- If a patient misses a dose, administer the missed dose as soon as possible, and then resume scheduled treatments every 3 or 4 weeks, as applicable.

Dose Adjustments for Measles Exposure

If a patient has been exposed to measles, it may be prudent to administer an extra dose of GAMMAGARD LIQUID ERC intravenously as soon as possible and within 6 days of exposure. A dose of 400 mg/kg should provide a serum level >240 milli–International Units (mIU)/mL of measles antibodies for at least two weeks.

If a patient is at risk of future measles exposure and receives a dose of less than 530 mg/kg every 3 to 4 weeks, the dose should be increased to at least 530 mg/kg. This should provide a serum level of 240 mIU/mL of measles antibodies for at least 22 days after infusion.

Subcutaneous Administration

- Prior to switching from IV to SC treatment, obtain the patient's serum IgG trough level to guide subsequent dose adjustments.
- Start the initial SC dose approximately one week after the last IV infusion.

Table 2: Recommended Dosage for Subcutaneous Administration
Dosage | Initial Infusion Rate | Maintenance Infusion Rate
Initial dose: Initial dose is 1.37 × previous IV dose divided by # of weeks between IV doses. Maintenance dose: Maintenance dose is based on clinical response and target IgG trough level. | 40 kg BW and greater: 30 mL/site at 20 mL/hr/site. Under 40 kg BW: 20 mL/site at 15 mL/hr/site. | 40 kg BW and greater: 30 mL/site at 20 to 30 mL/hr/site. Under 40 kg BW: 20 mL/site at 15 to 20 mL/hr/site.

Dose Adjustments

Based on the results of clinical studies with GAMMAGARD LIQUID, the expected increase in serum IgG trough level during weekly SC treatment at the dose adjusted to provide a comparable area under the curve (AUC), is approximately 281 mg/ deciliter (dL) higher than the last IgG trough level during prior stable IV treatment. To calculate the target trough IgG level for SC treatment, add 281 mg/dL to the IgG trough level obtained after the last IV treatment.

To guide dose adjustment, calculate the difference between the patient's target serum IgG trough level and the IgG trough level during SC treatment. Find this difference in the columns of Table 3 and the corresponding amount (in mL) by which to increase (or decrease) the weekly dose based on the patient's body weight. If the difference between measured and target trough levels is less than 100 mg/dL, then no adjustment is necessary. However, the patient's clinical response should be the primary consideration in dose adjustment.

Table 3: Change in Weekly Dose of GAMMAGARD LIQUID ERC and Difference Between Measured and Target IgG Trough Levels [Derived using a linear approximation to the nomogram method with a slope of 5.3 kg/dL.]
Body Weight | 100 mg/dL | 200 mg/dL | 300 mg/dL | 400 mg/dL
10 kg | 2 mL | 4 mL | 6 mL | 8 mL
20 kg | 4 mL | 8 mL | 11 mL | 15 mL
30 kg | 6 mL | 11 mL | 17 mL | 23 mL
40 kg | 8 mL | 15 mL | 23 mL | 30 mL
50 kg | 9 mL | 19 mL | 28 mL | 38 mL
60 kg | 11 mL | 23 mL | 34 mL | 45 mL
70 kg | 13 mL | 26 mL | 40 mL | 53 mL
80 kg | 15 mL | 30 mL | 45 mL | 60 mL
90 kg | 17 mL | 34 mL | 51 mL | 68 mL
100 kg | 19 mL | 38 mL | 57 mL | 75 mL
110 kg | 21 mL | 42 mL | 62 mL | 83 mL
120 kg | 23 mL | 45 mL | 68 mL | 91 mL
130 kg | 25 mL | 49 mL | 74 mL | 98 mL
140 kg | 26 mL | 53 mL | 79 mL | 106 mL

Example 1: A patient with a body weight of 80 kg has a measured IgG trough level of 800 mg/dL and the target trough level is 1000 mg/dL. The desired target trough level difference is 200 mg/dL (1000 mg/dL minus 800 mg/dL). The weekly dose of GAMMAGARD LIQUID ERC should be increased by 30 mL (3.0 g).

Example 2: A patient with a body weight of 60 kg has a measured IgG trough of 1000 mg/dL and the target trough level is 800 mg/dL. The desired target trough level difference is 200 mg/dL (800 mg/dL minus 1000 mg/dL). The weekly dose of GAMMAGARD LIQUID ERC should be decreased by 23 mL (2.3 g).

Dose Adjustments for Measles Exposure

If a patient has been exposed to measles, administer a dose of GAMMAGARD LIQUID ERC intravenously as soon as possible and within 6 days of exposure. A dose of 400 mg/kg IV should provide a serum level >240 mIU/mL of measles antibodies for at least two weeks.

If a patient is at risk of future measles exposure and receives a dose of less than 242 mg/kg subcutaneously per week, the dose should be increased to 242 mg/kg subcutaneously weekly while at risk.

2.2 Preparation and Handling

- Inspect the drug product visually for particulate matter and discoloration prior to administration. GAMMAGARD LIQUID ERC is a clear or slightly opalescent, colorless, or pale-yellow solution. Do not use if the solution is cloudy, turbid, or if it contains particulates.
- GAMMAGARD LIQUID ERC is for single-dose only. Partially used vials should be discarded. GAMMAGARD LIQUID ERC contains no preservatives.
- Allow refrigerated products to come to room temperature before use. DO NOT MICROWAVE.
- Do not shake.
- Do not mix with other products.
- Do not use normal saline as a diluent. If dilution is desired, 5% dextrose in water (D5W) should be used as a diluent.
- The infusion line may be flushed with normal saline. An in-line filter is optional.
- Record the name and lot number of the product in the recipient's records.

2.3 Administration

Intravenous Administration

- For rate of IV infusion, refer to Table 1
- Monitor patient vital signs throughout the infusion. Certain adverse reactions (ARs) such as headaches, flushing, and changes in pulse rate and blood pressure may be related to the rate of infusion. Slow or stop infusion if adverse reactions occur. If symptoms subside promptly, the infusion may be resumed at a lower rate that does not result in recurrence of the symptoms.
- Adverse reactions may occur more frequently in patients receiving immune globulin for the first time, upon switching brands or if there has been a long interval since the previous infusion. In such cases, start at lower infusion rates and gradually increase as tolerated.
- Ensure that patients with pre-existing renal insufficiency are not volume depleted. For patients over 65 years of age or judged to be at risk for renal dysfunction or thrombotic events, administer GAMMAGARD LIQUID ERC at the minimum infusion rate practicable. In such cases, the maximal rate should be less than 3.3 mg/kg/min (<2 mL/kg/hr); consider discontinuation of administration if renal function deteriorates [see Warnings and Precautions (5.2, 5.4), Use In Specific Populations (8.5)].

Subcutaneous Administration

Patients with a history of allergic reactions to immunoglobulin products should not be treated subcutaneously at home until 2 to 3 treatments have been administered and tolerated under medical supervision.

Selection of Infusion Site: Suggested areas for SC infusion of GAMMAGARD LIQUID ERC are abdomen, thighs, upper arms, or lower back. Infusion sites should be at least two inches apart, avoiding bony prominences. Rotate sites each week.

Volume per Site: The weekly dose (mL) should be divided by 30 or 20, based on patient weight above, to determine the number of sites required. Simultaneous SC infusion at multiple sites can be facilitated by using a multi-needle administration set.

Rate of Infusion

- For rate of SC infusion, refer to Table 2
- Patients 40 kg (88 lbs) and Greater: If multiple sites are used, the rate set on the pump should be the rate per site multiplied by the number of sites (e.g., 30 mL x 4 sites = 120 mL/hr). The number of simultaneous sites should be limited to 8, or maximum infusion rate of 240 mL/hr.
- Patients Under 40 kg (88 lbs): If multiple sites are used, the rate set on the pump should be the rate per site multiplied by the number of sites (e.g., 20 mL x 3 sites = 60 mL/hr). The number of simultaneous sites should be limited to 8, or maximum infusion rate of 160 mL/hr.

Instructions for Subcutaneous Administration: Instruct patients and/or caregivers to observe the following procedures:

1. Aseptic technique - Use aseptic technique when preparing and infusing GAMMAGARD LIQUID ERC.

2. Assemble supplies - Set up a clean work area and gather all supplies necessary for the SC infusion: vial(s) of GAMMAGARD LIQUID ERC, ancillary supplies, sharps container and pump. If GAMMAGARD LIQUID ERC has already been pooled into a bag or a syringe, skip to Step 6.

3. Product preparation - Remove the protective cap from the vial to expose the center of the vial (Figure 1).

Figure 1

4. Wipe the stopper – Wipe the stopper with an alcohol pad and allow it to dry (Figure 2).

Figure 2

5. Withdraw GAMMAGARD LIQUID ERC from the vials - Attach a sterile syringe to a needle and draw air into the syringe barrel equal to the amount of product to be withdrawn. Inject the air into the vial and withdraw the desired volume of GAMMAGARD LIQUID ERC (Figure 3). If multiple vials are required to achieve the desired dose, repeat this step.

Figure 3

6. Prepare the infusion pump and tubing - Follow the manufacturer's instructions for preparing the pump and administration tubing, if needed. Be sure to prime the pump tubing to ensure that no air is left in the tubing and needle.

7. Select the infusion sites - Select the number of infusion sites depending on the volume of the total dose. [see Table 2] for recommended maximum volumes and rates. Potential sites for infusion include the back of arms, abdomen, thighs, and lower back (Figure 4, Figure 5). Ensure sites are at least 2 inches apart; avoid bony prominences.

Figure 4

Figure 5

8. Cleanse the infusion site(s) - Cleanse the infusion site(s) with an antiseptic skin preparation (e.g., alcohol pad) using a circular motion working from the center of the site and moving to the outside. Allow to dry (Figure 6).

Figure 6

9. Insert the needle - Choose the correct needle length to assure that GAMMAGARD LIQUID ERC is delivered into the SC space. Grasp the skin and pinch at least one inch of skin between two fingers. Insert needle at a 90-degree angle with a darting motion into the SC tissue. Secure the needle (Figure 7).

Figure 7

10. Check for proper needle placement - Prior to the start of infusion, check each needle for correct placement to make sure that a blood vessel has not been punctured. Gently pull back on the attached syringe plunger and monitor for any blood return in the needle set. If you see any blood, remove and discard the needle set. Repeat priming and needle insertion steps in a different infusion site with a new needle set (Figure 8).

Figure 8

11. Secure the needle to the skin - Secure the needle(s) in place by applying a sterile protective dressing over the site (Figure 9).

Figure 9

12. Start the infusion of GAMMAGARD LIQUID ERC - Follow the manufacturer's instructions to turn the pump on (Figure 9).

13. Document the infusion - Remove the peel-off label with product lot number and expiration date from the GAMMAGARD LIQUID ERC vial and place in treatment diary/logbook to keep track of the product lots used. Keep the treatment diary/logbook current by recording the time, date, dose, product label and any reactions after each infusion.

14. Remove needle set - After the infusion is complete, remove the needle set and gently press a small piece of gauze over the needle insertion site and cover with a protective dressing. Discard any unused solution and disposable supplies in accordance with local requirements.

3 DOSAGE FORMS AND STRENGTHS

GAMMAGARD LIQUID ERC is available as an immune globulin (Human) 10% (100 mg/mL) solution with less than or equal to 2 µg/mL immunoglobulin A (IgA).

GAMMAGARD LIQUID ERC is available in a 50 mL and 100 mL single-dose vial.

4 CONTRAINDICATIONS

GAMMAGARD LIQUID ERC is contraindicated in patients who have a history of anaphylactic or severe systemic hypersensitivity reactions to the administration of GAMMAGARD LIQUID ERC [see Warnings and Precautions (5.1)].

5 WARNINGS AND PRECAUTIONS

5.1 Hypersensitivity Reactions

Severe hypersensitivity reactions may occur after treatment with immune globulin products, including GAMMAGARD LIQUID ERC, even in patients previously treated with immune globulin products. Patients with known antibodies to IgA may have a greater risk of developing potentially severe hypersensitivity and anaphylactic reactions. In case of severe hypersensitivity, discontinue GAMMAGARD LIQUID ERC infusion immediately and manage with appropriate medications which may include epinephrine for immediate treatment.

GAMMAGARD LIQUID ERC contains IgA less than or equal to 2 µg/mL in a 10% solution. The concentration of IgA that will not provoke a reaction is not known, and therefore all immunoglobulin products, including GAMMAGARD LIQUID ERC, carry the risk of inducing an anaphylactic reaction to IgA.

5.2 Renal Injury

Renal injury including acute renal failure, acute tubular necrosis, proximal tubular nephropathy, and osmotic nephrosis may occur after treatment with immune globulin products, including GAMMAGARD LIQUID ERC.

Ensure patients are not volume depleted before administering GAMMAGARD LIQUID ERC. In patients who are at risk of renal injury because of pre-existing renal insufficiency or predisposition to acute renal failure (such as diabetes mellitus, age greater than 65, volume depletion, sepsis, paraproteinemia, or patients receiving known nephrotoxic drugs, etc.), administer GAMMAGARD LIQUID ERC at the minimum rate of infusion practicable [see Dosage and Administration (2.3)].

Assess renal function, including measurement of blood urea nitrogen (BUN), serum creatinine, and urine output in patients receiving GAMMAGARD LIQUID ERC prior to initial infusion and at appropriate intervals thereafter. If renal function deteriorates, consider discontinuation of GAMMAGARD LIQUID ERC [see Dosage and Administration (2.3)].

5.3 Hyperproteinemia, Hyperviscosity, and Hyponatremia

Hyperproteinemia, hyperviscosity, and hyponatremia may occur in patients receiving immune globulin products, including GAMMAGARD LIQUID ERC. Distinguish true hyponatremia from pseudohyponatremia that is temporally or causally related to hyperproteinemia with concomitant decreased calculated serum osmolality or elevated osmolar gap. Treatment aimed at decreasing serum free water in patients with pseudohyponatremia may lead to volume depletion and hyperviscosity and a predisposition to thromboembolic events.

5.4 Thrombosis

Thrombosis may occur following treatment with immune globulin products, including GAMMAGARD LIQUID ERC. Risk factors include advanced age, prolonged immobilization, hypercoagulable conditions, history of venous or arterial thrombosis, use of estrogens, indwelling central vascular catheters, hyperviscosity, and cardiovascular risk factors. Thrombosis may occur in the absence of known risk factors.

Ensure adequate hydration in patients before administration of GAMMAGARD LIQUID ERC. For patients at risk of thrombosis, administer GAMMAGARD LIQUID ERC at the minimum dose and infusion rate practicable. Monitor patients for signs and symptoms of thrombosis.

Consider baseline assessment of blood viscosity in patients at risk for hyperviscosity, including patients with cryoglobulins, fasting chylomicronemia, high triacylglycerols (triglycerides), or monoclonal gammopathies [see Boxed Warning, Dosage and Administration (2.3)].

5.5 Aseptic Meningitis Syndrome

Aseptic meningitis syndrome (AMS) may occur with immune globulin products, including GAMMAGARD LIQUID ERC. The risk of AMS may be higher with high doses (2 g/kg) and/or rapid infusion of immunoglobulin products. Signs and symptoms of AMS include severe headache, nuchal rigidity, drowsiness, fever, photophobia, painful eye movements, nausea and vomiting. AMS usually begins within several hours to 2 days following immune globulin treatment. Conduct neurological examination on patients exhibiting symptoms and signs of AMS, including Cerebrospinal fluid (CSF) studies, to rule out other causes of meningitis. CSF studies frequently reveal pleocytosis up to several thousand cells per cubic millimeter, elevated protein levels up to several hundred mg/dL, and negative culture results. Discontinuation of immune globulin treatment has resulted in remission of AMS within several days without sequelae.

5.6 Hemolysis

Hemolysis may occur with immune globulin products, including GAMMAGARD LIQUID ERC due to the presence of blood group antibodies that may act as hemolysins and induce in vivo coating of red blood cells (RBC). This may cause a positive direct antiglobulin test [DAT (Coombs test)]. Delayed hemolytic anemia can develop after GAMMAGARD LIQUID ERC therapy due to enhanced RBC sequestration [see Adverse Reactions (6)].

The risk factors for hemolysis include high doses (e.g., ≥2 g/kg, either as a single administration or divided over several days), non-O blood group, and underlying inflammatory disease condition.

Monitor patients for signs and symptoms of hemolysis. Conduct appropriate laboratory testing in higher risk patients, including measurement of hemoglobin or hematocrit prior to infusion and within approximately 36 to 96 hours post-infusion. If signs and symptoms of hemolysis are observed, perform additional confirmatory laboratory testing [see Warnings and Precautions (5.9)].

5.7 Transfusion-Related Acute Lung Injury

Transfusion-Related Acute Lung Injury (TRALI) may occur following treatment with immune globulin products, including GAMMAGARD LIQUID ERC. Symptoms typically occur within 1 to 6 hours after treatment and may include severe respiratory distress, pulmonary edema, hypoxemia, normal left ventricular function, and fever.

Monitor patients for signs and symptoms of TRALI. If TRALI is suspected, perform appropriate tests for the presence of anti-neutrophil and anti-HLA antibodies in both the product and patient serum. Manage patients using oxygen therapy with ventilatory support as appropriate.

5.8 Transmission Infectious Agents

There is risk of transmission of infectious disease or agents including viruses, the variant Creutzfeldt-Jakob disease (vCJD) agent, and the Creutzfeldt-Jakob disease agent with GAMMAGARD LIQUID ERC administration because it is manufactured using human blood. The risk of infectious agent transmission is minimized by plasma donor screening, donation testing, and manufacturing steps proven to inactivate and remove bloodborne pathogens.

All infections thought by a physician to possibly have been transmitted by this product should be reported by to Takeda Pharmaceuticals U.S.A., Inc at 1-877-TAKEDA-7 (1-877-825-3327) (in the U.S.).

5.9 Monitoring Laboratory Tests

- Assess renal function including measurement of blood urea nitrogen (BUN) and serum creatinine before the initial infusion of GAMMAGARD LIQUID ERC and at appropriate intervals thereafter.
- Consider baseline assessment of blood viscosity in patients at risk for hyperviscosity, including those with cryoglobulins, fasting chylomicronemia, high triacylglycerols (triglycerides), or monoclonal gammopathies, because of the potentially increased risk of thrombosis.
- If signs and/or symptoms of hemolysis are present after an infusion of GAMMAGARD LIQUID ERC, perform appropriate laboratory testing for confirmation.
- If TRALI is suspected, perform appropriate tests for the presence of anti-neutrophil antibodies and anti-HLA antibodies in both the product and the patient's serum.

5.10 Interference with Laboratory Tests

False positive serological testing results including a positive direct or indirect antiglobulin (Coombs) test may occur after administration of immune globulin products, including GAMMAGARD LIQUID ERC due to the transitory rise of various passively transferred antibodies.

Administration of immune globulin products, including GAMMAGARD LIQUID ERC, can lead to false positive readings in assays that depend on detection of beta-D-glucans for diagnosis of fungal infections; this may persist during the weeks following infusion of the product.

6 ADVERSE REACTIONS

6.1 Clinical Trials Experience

Because clinical studies are conducted under widely varying conditions, adverse reaction rates observed in the clinical studies of a drug cannot be directly compared to rates in the clinical studies of another drug and may not reflect the rates observed in practice.

No clinical studies have been conducted using GAMMAGARD LIQUID ERC. The safety of GAMMAGARD LIQUID ERC in patients with primary humoral immunodeficiency (PI) is supported by two clinical studies conducted on GAMMAGARD LIQUID, Study 1 and Study 2 as described below.

Study 1

The safety of GAMMAGARD LIQUID IV infusion was evaluated in Study 1. A total of 61 patients received 1,811 infusions of GAMMAGARD LIQUID at a dose of 300 to 600 mg/kg every 21 to 28 days for 12 months [see Clinical Studies 14].

A total of 5 serious adverse reactions were reported in 4 patients (28%), including two cases of aseptic meningitis in one patient, stent placement, gastrointestinal hemorrhage, and encephalopathy. Out of these 5 serious adverse reactions, only 1 case of aseptic meningitis was deemed to be related by the investigator. Two patients were discontinued, likely due to adverse reactions, which were pruritic papular rash and aseptic meningitis.

Table 4: summarizes the most common adverse reactions occurring in ≥5% of patients in Study 1.

Table 4: Adverse Reactions Occurring in ≥5% of Patients in Study 1
Adverse Reactions [Adverse reactions were defined as adverse events occurring during or within 72 hours of infusion or any causally related event occurring within the study period.] | By Infusion N (%) (N=1,811 Infusions) | By Patient N (%) (N=61 Patients)
Headache | 94 (5%) | 29 (48%)
Fatigue | 33 (2%) | 14 (23%)
Pyrexia | 28 (2%) | 17 (28%)
Chills | 28 (2%) | 12 (20%)
Nausea | 17 (0.9%) | 11 (18%)
Pain in extremity | 13 (0.7%) | 7 (11%)
Diarrhea | 12 (0.7%) | 9 (15%)
Migraine | 12 (0.7%) | 4 (7%)
Vomiting | 11 (0.6%) | 9 (15%)
Dizziness | 11 (0.6%) | 8 (13%)
Urticaria | 10 (0.6%) | 6 (10%)
Cough | 9 (0.5%) | 8 (13%)
Asthma | 7 (0.4%) | 6 (10%)
Oropharyngeal pain | 7 (0.4%) | 5 (8%)
Infusion site extravasation | 7 (0.4%) | 4 (7%)
Arthralgia | 6 (0.3%) | 5 (8%)
Rash | 6 (0.3%) | 4 (7%)
Myalgia | 5 (0.3%) | 5 (8%)
Pruritus | 5 (0.3%) | 4 (7%)
Cardiac murmur | 4 (0.2%) | 4 (7%)

Study 2

The safety of GAMMAGARD LIQUID SC infusion was evaluated in Study 2. A total of 47 patients received 2,294 SC infusions of GAMMAGARD LIQUID at a mean dose of 182 to 191 mg/kg/week for a median duration of 379 days (range 57 to 477 days) [see Clinical Studies 14].

One serious adverse reaction of chest pain was reported in 1 patient (2%). One patient discontinued likely due to adverse reactions of fatigue and malaise.

Table 5 summarizes the most common adverse reactions occurring in ≥5% of patients in Study 2.

Table 5: Adverse Reactions Occurring in ≥5% of Patients in Study 2
Adverse Reactions [Adverse reactions were defined as adverse events occurring during or within 72 hours of infusion or any causally related event occurring within the study period.] | By Infusion N (%) (N=2294 Infusions) | By Patient N (%) (N=47 Patients)
Infusion site (local) event [included rash, erythema, edema, hemorrhage, pain, hematoma, pruritus, and swelling.] | 55 (2%) | 21 (45%)
Headache | 31 (1%) | 19 (40%)
Pyrexia | 11 (0.5%) | 9 (19%)
Fatigue | 11 (0.5%) | 7 (15%)
Heart rate increased | 11 (0.5%) | 3 (6%)
Abdominal pain upper | 9 (0.4%) | 5 (11%)
Vomiting | 7 (0.3%) | 5 (11%)
Arthralgia | 7 (0.3%) | 3 (6%)
Nausea | 7 (0.3%) | 3 (6%)
Asthma | 6 (0.3%) | 4 (9%)
Blood pressure systolic increased | 6 (0.3%) | 3 (6%)
Diarrhea | 5 (0.2%) | 3 (6%)
Ear pain | 4 (0.2%) | 3 (6%)
Aphthous ulcer | 3 (0.1%) | 3 (6%)
Migraine | 3 (0.1%) | 3 (6%)
Oropharyngeal pain | 3 (0.1%) | 3 (6%)
Pain in extremity | 3 (0.1%) | 3 (6%)

6.2 Postmarketing Experience

Because adverse reactions are reported voluntarily post-approval from a population of uncertain size, it is not always possible to reliably estimate their frequency or establish a causal relationship to product exposure.

GAMMAGARD LIQUID

The following adverse reactions have been identified during postmarketing use of GAMMAGARD LIQUID.

Intravenous Administration

Blood and Lymphatic System Disorders: Hemolysis

Immune System Disorders: Anaphylactic shock

Nervous System Disorders: Cerebral vascular accident, Transient ischemic attack, Tremor

Cardiac Disorders: Myocardial infarction

Vascular Disorders: Deep vein thrombosis, Hypotension

Respiratory, Thoracic and Mediastinal Disorders: Pulmonary embolism, Pulmonary edema, Chest pain, Transfusion-related acute lung injury

Skin and Subcutaneous Tissue Disorders: Hyperhidrosis

Investigations: Coombs direct test positive, Oxygen saturation decreased

Subcutaneous Administration

Immune System Disorders: Hypersensitivity

Musculoskeletal and Connective Tissue Disorders: Myalgia

General Disorders and Administration Site Conditions: Chills

GENERAL

In addition to the adverse reactions listed above, the following adverse reactions have been identified for immune globulin products.

Blood and Lymphatic System Disorder: Hemolytic anemia, Pancytopenia

Nervous System Disorders: Aseptic meningitis, Coma, Seizures, Loss of consciousness, Paresthesia, Lethargy

Cardiac Disorders: Arrhythmia, Tachycardia, Cardiac arrest

Vascular Disorders: Flushing, Vascular collapse

Respiratory, Thoracic and Mediastinal Disorders: Cyanosis, Hypoxemia, Bronchospasm, Apnea, Acute Respiratory Distress Syndrome (ARDS), Dyspnea, Laryngospasm, Renal and Urinary Disorders: Renal impairment, Osmotic nephropathy

Skin and Subcutaneous Tissue Disorders: Bullous dermatitis, Epidermolysis, Erythema multiforme, Stevens-Johnson Syndrome

Gastrointestinal Disorders: Hepatic dysfunction

General Disorders and Administration Site Conditions: Malaise, Fever, Injection site reaction (including induration, warmth)

7 DRUG INTERACTIONS

Immunoglobulin administration may transiently impair the efficacy of live attenuated virus vaccines such as mumps, rubella and varicella because of passively acquired antibodies. Inform the immunizing physician of recent therapy with GAMMAGARD LIQUID ERC so that appropriate precautions can be taken.

8 USE IN SPECIFIC POPULATIONS

8.1 Pregnancy

Risk Summary

Animal reproduction studies have not been conducted with GAMMAGARD LIQUID ERC. It is not known whether GAMMAGARD LIQUID ERC can cause fetal harm when administered to a pregnant woman or can affect reproduction capacity. Immune globulins cross the placenta from maternal circulation increasingly after 30 weeks of gestation. GAMMAGARD LIQUID ERC should be given to a pregnant woman only if clearly indicated.

The background risk of major birth defects and miscarriage for the indicated population is unknown. In the U.S. general population, the estimated background risk of major birth defects and miscarriage in clinically recognized pregnancies is 2 to 4% and 15 to 20%, respectively.

8.2 Lactation

Risk Summary

There is no information regarding the presence of GAMMAGARD LIQUID ERC in human milk, its effects on the breast-fed infant or its effects on milk production. The developmental and health benefits of breastfeeding should be considered along with the mother's clinical need for GAMMAGARD LIQUID ERC and any potential adverse effects on the breast-fed infant from GAMMAGARD LIQUID ERC or from the underlying maternal condition.

8.4 Pediatric Use

GAMMAGARD LIQUID clinical studies have established the safety and efficacy of the GAMMAGARD LIQUID ERC in pediatric patients with PI aged 2 years of age and older.

GAMMAGARD LIQUID administered intravenously was evaluated in 15 pediatric patients with PI (7 patients aged 2 to <12 years and 8 patients aged 12 to <16 years). GAMMAGARD LIQUID administered subcutaneously was evaluated in 18 pediatric patients with PI (14 patients aged 2 to <12 years and 4 patients aged 12 to <16 years) [see Adverse Reactions (6) and Clinical Studies (14)].

The safety and efficacy of GAMMAGARD LIQUID ERC in pediatric patients below the age of 2 have not been established.

8.5 Geriatric Use

Limited information is available for the geriatric use of GAMMAGARD LIQUID ERC. The geriatric use of GAMMAGARD LIQUID administered intravenously and subcutaneously was evaluated in two clinical studies (Study 1 and Study 2). The studies included 8 patients over the age of 65 years. No differences in safety or efficacy were observed for this group. Monitor patients who are at an increased risk for developing renal failure or thrombotic events. Do not exceed the recommended dose. Infuse at the minimum IV infusion rate practicable [see Boxed Warning, Warnings and Precautions (5.2, 5.4), Dosage and Administration (2.3)].

10 OVERDOSAGE

With IV administration, an overdose of GAMMAGARD LIQUID ERC may lead to fluid overload and hyperviscosity. Patients at risk of complications of fluid overload and hyperviscosity include elderly patients and those with cardiac or renal impairment.

11 DESCRIPTION

GAMMAGARD LIQUID ERC (human immunoglobulin) is a single-dose sterile, liquid preparation of purified and concentrated IgG antibodies. GAMMAGARD LIQUID ERC has an IgA concentration less than or equal to 2 µg/mL, in a 10% solution.

The distribution of the IgG subclasses is similar to that of normal plasma with lower levels of IgG4 and IgG3. The Fc and Fab functions are maintained in GAMMAGARD LIQUID ERC. Pre-kallikrein activator activity is not detectable. GAMMAGARD LIQUID ERC contains 100 mg/mL protein. At least 98% of the protein is immune globulin, the average IgA concentration is less than or equal to 2 µg/mL, in a 10% solution and immunoglobulin M is present in trace amounts.

GAMMAGARD LIQUID ERC contains a broad spectrum of IgG antibodies against bacterial and viral agents. Glycine (0.25M) serves as a stabilizing and buffering agent. There are no added sugars, sodium, or preservatives. The pH is 4.6 to 5.1. The osmolality is 240 to 300 mOsmol/kg, which is similar to physiological osmolality (285 to 295 mOsmol/kg).

GAMMAGARD LIQUID ERC is manufactured from large pools of human plasma. IgG preparations are purified from plasma pools using a modified Cohn-Oncley cold ethanol fractionation process, as well as cation and anion exchange chromatography. GAMMAGARD LIQUID ERC shares its manufacturing process with GAMMAGARD LIQUID. The differentiation occurs with the modified parameters applied during the anion exchange chromatography step enhanced removal capability (ERC) to reduce IgA content, resulting in a product with IgA less than or equal to 2 µg/mL in a 10% solution.

Screening against potentially infectious agents begins with the donor selection process and continues throughout plasma collection and plasma preparation. Each individual plasma donation used in the manufacture of GAMMAGARD LIQUID ERC is collected only at FDA-approved blood establishments and is tested by FDA licensed serological tests for Hepatitis B Surface Antigen (HBsAg), and for antibodies to Human Immunodeficiency Virus (HIV-1/HIV-2) and Hepatitis C Virus (HCV) in accordance with U.S. regulatory requirements. As an additional safety measure, mini-pools of the plasma are tested for the presence of HIV-1 and HCV by FDA licensed Nucleic Acid Testing (NAT) and found to be negative.

To improve the margin of safety, validated virus inactivation/removal steps have been integrated into the manufacturing and formulation processes, namely solvent/detergent (S/D) treatment, nanofiltration, and a low pH incubation at elevated temperature (30° to 32°C). The S/D process includes treatment with an organic mixture of tri-n-butyl phosphate, octoxynol 9 and polysorbate 80 at 18° to 25°C for a minimum of 60 minutes. S/D treatment inactivates the lipid-enveloped viruses investigated to below detection limits within minutes.

In vitro virus spiking studies have been used to validate the capability of the manufacturing process to inactivate and remove viruses. To establish the minimum applicable virus clearance capacity of the manufacturing process, virus clearance studies were performed under extreme conditions (e.g., at minimum S/D concentrations, incubation time and temperature for the S/D treatment).

Virus clearance studies for GAMMAGARD LIQUID ERC performed in accordance with good laboratory practices are summarized in Table 6.

Table 6: Three Dedicated Independent Virus Inactivation/Removal Steps, Mean Log10 Reduction Factors [For the calculation of these RF data from virus clearance study reports, applicable manufacturing conditions were used. Log10 RFs on the order of 4 or more are considered effective for virus clearance in accordance with the Committee for Medicinal Products for Human Use (CHMP, formerly CPMP) guidelines.] (RFs) for Each Virus and Manufacturing Step
Virus Type | Enveloped RNA |  |  | Enveloped DNA | Non-enveloped RNA |  | Non-enveloped DNA
Family | Retroviridae | Flaviviridae |  | Herpesviridae | Picornaviridae |  | Parvoviridae
Virus | HIV-1 | BVDV | WNV | PRV | HAV | EMCV | MMV
SD treatment | >4.5 | >6.2 | n.a. | >4.8 | n.d. | n.d. | n.d.
Nanofiltration | >4.5 | >5.1 | >6.2 | >5.6 | 5.7 | 1.4 | 2.0
Low pH treatment | >5.8 | >5.5 | >6.0 | >6.5 | n.d. [No RF obtained due to immediate neutralization of HAV by the anti-HAV antibodies present in the product.] | >6.3 | 3.1
Overall log reduction factor (ORF) | >14.8 | >16.8 | >12.2 | >16.9 | 5.7 | >7.7 | 5.1
Abbreviations: HIV-1, Human Immunodeficiency Virus Type 1; BVDV, Bovine Viral Diarrhea Virus (model for Hepatitis C Virus and other lipid enveloped RNA viruses); WNV, West Nile Virus; PRV, Pseudorabies Virus (model for lipid enveloped DNA viruses, including Hepatitis B Virus); EMCV, Encephalomyocarditis Virus (model for non-lipid enveloped RNA viruses, including Hepatitis A Virus [HAV]); MMV, Mice Minute Virus (model for non-lipid enveloped DNA viruses, including B19 Virus [B19V]); n.d. (not done), n.a. (not applicable).

12 CLINICAL PHARMACOLOGY

12.1 Mechanism of Action

GAMMAGARD LIQUID ERC supplies a broad spectrum of opsonizing and neutralizing IgG antibodies against a wide variety of bacterial and viral agents. GAMMAGARD LIQUID ERC also contains a spectrum of antibodies capable of interacting with and altering the activity of cells of the immune system as well as antibodies capable of reacting with cells such as erythrocytes. The role of these antibodies and the mechanism of action of IgG in GAMMAGARD LIQUID ERC have not been fully elucidated.

12.3 Pharmacokinetics

Study 1

Following IV infusion, IGIV products show a biphasic decay curve. The initial (α) phase is characterized by an immediate post-infusion peak in serum IgG and is followed by rapid decay due to equilibration between the plasma and extravascular fluid compartments. The second (β) phase is characterized by a slower and constant rate of decay.

The pharmacokinetics of immunoglobulins depend on their concentration.

The commonly cited "normal" half-life of 18 to 25 days is based on studies in which tiny quantities of radiolabeled IgG are injected into healthy individuals. When radiolabeled IgG was injected into patients with hypogammaglobulinemia or agammaglobulinemia, highly variable half-lives ranging from 12 to 40 days were observed. In other radiolabeled studies, high serum concentrations of IgG and hypermetabolism associated with fever and infection have been seen to coincide with a shortened IgG half-life.

In contrast, pharmacokinetic studies of GAMMAGARD LIQUID in immunodeficient patients are based on the decline of IgG concentrations following infusion of large quantities of immune globulin. In such studies, investigators have reported uniformly prolonged half-lives of 26 to 35 days. Pharmacokinetic parameters for GAMMAGARD LIQUID were determined from total IgG levels following the fourth infusion in patients with primary humoral immunodeficiency (N=61) treated intravenously with the product every 3 or 4 weeks according to the regimen used prior to entering the study. Of these, 57 had sufficient pharmacokinetic data to be included in the dataset. The median weight-adjusted dose per patient was 455 mg/kg/4 weeks with a range of 262 to 710 mg/kg/4 weeks. Pharmacokinetic parameters are presented in Table 7.

Table 7: Summary of Intravenous Pharmacokinetic Parameters in 57 Patients
Parameter | Median | 95% Confidence Interval
Dose of IgG (mg/kg/4 weeks) | 455 | Range: 262 to 710
Elimination Half-Life (T1/2 days) | 35 | (31, 42)
AUC0-21d (milligram days/dL) | 29139 | (27494, 30490)
Cmax (Peak, mg/dL) | 2050 | (1980, 2200)
Cmin (Trough, mg/dL) | 1030 | (939, 1110)
Incremental recovery (mg/dL)/(mg/kg) | 2.3 | (2.2, 2.6)
Abbreviations: AUC=area under the curve, Cmax=maximum concentration, Cmin=minimum concentration

Median IgG trough levels were maintained between 960 to 1120 mg/dL. These dosing regimens-maintained serum trough IgG levels generally considered adequate to prevent bacterial infections. The elimination of half-life of GAMMAGARD LIQUID (35 days) was similar to that reported for other IGIV products.

Study 2

Pharmacokinetic (PK) parameters of subcutaneously administered GAMMAGARD LIQUID were evaluated in patients with primary immunodeficiency (PI) who were 12 years of age and older during a clinical study [see Clinical Studies (14)].

Patients were treated intravenously for 12 weeks with GAMMAGARD LIQUID and then switched to weekly SC GAMMAGARD LIQUID infusions. Initially, all patients were treated for a minimum of 12 weeks at a SC dose that was 130% of the IV dose. A comparison of the AUC for IV and SC infusions done on the first 15 adult patients determined that the SC dose required to provide an exposure from SC administration that was not inferior to the exposure from IV administration was 137% of the IV dose. Subsequently, all patients were treated with this dose for 6 weeks after which the dose was individualized for all patients based on IgG trough levels, as described below. After a minimum of 8 weeks at this SC dose, a PK evaluation was conducted on patients 12 years of age or older (N=32).

The mean adjusted dose at the end of the study was 137.3% (125.7 to 150.8) of the IV dose for patients 12 years of age and older, and 141.0% (100.5 to 160.0) for patients under the age of 12. Thus, a significant dosing difference was not required for children. At this dose adjustment, the geometric mean ratio of the AUC for SC vs IV GAMMAGARD LIQUID administration was 95.2% (90% confidence limit (CI): 92.3 to 98.2). The peak IgG level occurred 2.9 (1.2 to 3.2) days after SC administration.

Pharmacokinetic parameters of GAMMAGARD LIQUID administered intravenously vs subcutaneously in clinical study are shown in Table 8. The mean peak IgG level was lower (1393 ± 289 mg/dL) during SC treatment than with IV treatment (2240 ± 536 mg/dL), consistent with lower weekly doses compared with doses administered every 3 or 4 weeks intravenously. In contrast, the mean trough level was higher when GAMMAGARD LIQUID was given subcutaneously (1202 ± 282 mg/dL) than when it was given intravenously (1050 ± 260 mg/dL), a result of both higher monthly dose and more frequent dosing. The median IgG trough level during IV treatment in this clinical study, 1010 mg/dL (95% CI: 940 to 1240), was similar to the median IgG trough level of 1030 mg/dL (95% CI: 939 to 1110) during IV treatment as shown in Table 8. By contrast, the median IgG trough level during SC treatment was higher, at 1260 mg/dL (95% CI: 1060 to 1400).

Table 8: Pharmacokinetic Parameters of Subcutaneously Administered GAMMAGARD LIQUID Compared with GAMMAGARD LIQUID Administered Intravenously in 32 Patients
Pharmacokinetic Parameters |  | Subcutaneous Administration | Intravenous Administration
Dose [Weekly equivalent dose] (mg/kg) | Mean ± SD | 182.6 ± 48.4 | 133.2 ± 36.9
Dose [Weekly equivalent dose] (mg/kg) | Range (min to max) | 94.2 to 293.8 | 62.7 to 195.4
IgG Peak Levels (mg/dL) | Mean ± SD | 1393 ± 289 | 2240 ± 536
IgG Peak Levels (mg/dL) | Range (min to max) | 734 to 1900 | 1130 to 3610
IgG Trough Levels (mg/dL) | Mean ± SD | 1202 ± 282 | 1050 ± 260
IgG Trough Levels (mg/dL) | Range (min to max) | 621 to 1700 | 532 to 1460
AUC (days [Standardized to a 7-day interval] mg/dL) | Mean ± SD | 9176 ± 1928 | 9958 ± 2274
AUC (days [Standardized to a 7-day interval] mg/dL) | Range (min to max) | 4695 to 12468 | 5097 to 13831
Clearance (mL/kg/day) | Mean ± SD | 2.023 ± 0.528 | 1.355 ± 0.316
Clearance (mL/kg/day) | Range (min to max) | 1.225 to 3.747 | 0.880 to 2.340

13 NONCLINICAL TOXICOLOGY

13.1 Carcinogenesis, Mutagenesis, Impairment of Fertility

An in vitro mutagenicity test was performed with GAMMAGARD LIQUID. No evidence of mutagenicity was observed.

13.2 Animal Toxicology and/or Pharmacology

In single-dose toxicity studies GAMMAGARD LIQUID revealed no adverse effects at doses of 5000 mg/kg or 2000 mg/kg in mice and rats, respectively. Repeat-dose toxicity studies were not conducted.

In in-vitro immune cell activation, cytokine/chemokine release and complement activation assays with GAMMAGARD LIQUID ERC no increased potential to stimulate the immune system and associated risk for hypersensitivity reactions compared to GAMMAGARD LIQUID were revealed. No hypotensive or bronchospastic effects were observed with GAMMAGARD LIQUID ERC in safety pharmacology studies in spontaneously hypertensive rats and guinea pigs.

14 CLINICAL STUDIES

No clinical studies have been conducted with GAMMAGARD LIQUID ERC. The efficacy of GAMMAGARD LIQUID ERC for primary humoral immunodeficiency (PI) are supported by two clinical studies conducted on GAMMAGARD LIQUID, Study 1 with IV administration (NCT00157079) and Study 2 with both IV and SC administration (NCT00546871).

Study 1 (NCT00157079)

This was an open-label study to evaluate the efficacy of GAMMAGARD LIQUID in patients with PI. A total of 61 patients received IV infusion of GAMMAGARD LIQUID at the dose 300 to 600 mg/kg every 21 to 28 days for 12 months.

The population characteristics were as follows: The median age was 34 years (range 6 to 72 years), 54% were female 93% were Caucasian, 5% were African American, and 2% were Asian. Three patients were excluded from the per-protocol efficacy analysis due to study withdrawal for non-study product related reasons.

The primary efficacy outcome was the annualized rate of acute serious bacterial infections defined as the mean number of prespecified acute serious bacterial infections per patient per year. Secondary efficacy outcome measure was hospitalizations secondary to infection. Table 9 summarizes the efficacy results.

Table 9: Efficacy Outcomes from Study 1 (N=58)
Efficacy Outcomes | Number of Events
Serious Acute Bacterial Infections [Serious acute bacterial infections were defined by FDA and met specific diagnostic requirements]
Bacteremia/Sepsis | 0
Bacterial Meningitis | 0
Osteomyelitis/Septic Arthritis | 0
Bacterial Pneumonia | 0
Visceral Abscess | 0
Total | 0
Hospitalizations Secondary to Infection | 0
Mean Number of Validated Infections per Patient per Year | 0
p-value [The rate of validated infections was compared with a rate of 1 per patient per year, in accordance with recommendations by the FDA Blood Products Advisory Committee] | p<0.0001
95% Confidence Interval | (0.000, 0.064)

Study 2 (NCT00546871)

An open-label, non-controlled, multicenter study to determine the efficacy, tolerability and PK of GAMMAGARD LIQUID SC infusion in adult and pediatric patients with PI.

A total of 49 patients were treated for 12 weeks with GAMMAGARD LIQUID IV infusion every 3 or 4 weeks. Patients who were on IV treatment prior to entering the study were switched to GAMMAGARD LIQUID at the same dose and frequency. Patients who were receiving SC immune globulin were switched to GAMMAGARD LIQUID at the IV dose they had received prior to switching to SC treatment. A PK analysis was performed at the end of the IV period in all patients aged 12 years and older. One week after the last IV infusion, each patient began SC treatment with GAMMAGARD LIQUID at 130% of the weekly equivalent of the IV dose for a minimum of 12 weeks. The median dose determined from the PK studies of the first 15 adult patients exposed to SC treatment was 137% of the IV dose, and subsequently all patients were treated for a minimum of 6 weeks at this dose. After 6 SC infusions, a trough IgG level was obtained and used to individually adapt the SC dose of GAMMAGARD LIQUID to compensate for individual variation [see Clinical Pharmacology (12.3)]. All patients received a minimum of 12 infusions at this individually adapted dose and continued to receive SC treatment with GAMMAGARD LIQUID until the last patient completed the study. Patients (N=47) were treated with 2,294 SC infusions of GAMMAGARD LIQUID: 4 patients treated for up to 29 weeks, 17 patients for 30 to 52 weeks, and 26 patients for 53 weeks or longer. Two patients that completed the IV treatment part of the study did not continue to the SC treatment part of the study. The median duration of SC treatment was 379 days (range: 57 to 477 days).

The population characteristics were as follows: The median age was 20 years (range 3 to 77 years) including 18 pediatric patients, 45% were female, 94% were Caucasian, 4% were Black, and 2% were Hispanic.

Mean weekly SC doses ranged from 182 mg/kg to 191 mg/kg (at 130% to 137% of the IV dose). In the study, the number of infusion sites per infusion was dependent on the dose of IgG and ranged from 2 to 10. In 75% of infusions, the number of infusion sites was 5 or fewer.

The efficacy results are summarized in Table 10 below.

Table 10: Efficacy Outcomes from Study 2 (N = 47) during Subcutaneous Treatment
Infections
Number of patients (efficacy phase) Total number of patients years Number of patients with serious bacterial infections Number of serious bacterial infections Annual rate of serious bacterial infections Annual rate of any infections | 47 44 3 3 (all bacterial pneumonias) 0.07 (99% upper CI 0.13) [CI is lower than the minimal goal of achieving a rate of <1 bacterial infection per patient-year] infections/patient year 4 (95% CI 3 to 5) infections/patient year
Antibiotic use [Included systemic and topical antibacterial, anti-fungal, anti-viral, and anti-protozoal antimicrobials.] (prophylaxis or treatment)
Number of patients (%) Annual rate | 40 (85%) 50 (95% CI 33 to 72) days/patient year
Days out of work/school/day care or unable to perform normal activities
Number of patients (%) Annual rate | 25 (53%) 4 (95% CI 2 to 6) days/patient year
Hospitalizations due to infections
Number of patients (%) Annual rate | 0 (0%) 0 (95% CI 0.0 to 0.1) days/patient year

16 HOW SUPPLIED/STORAGE AND HANDLING

GAMMAGARD LIQUID ERC is supplied in single-dose vials containing the labeled amount of functionally active IgG with less than or equal to 2 μg/mL IgA in a 10% solution.

The packaging of this product is not made with natural rubber latex.

The following presentations of GAMMAGARD LIQUID ERC are available:

NDC Number (Carton) | NDC Number (Vial) | Volume | Protein
0944-2705-50 | 0944-2705-05 | 50 mL | 5 g
0944-2705-10 | 0944-2705-01 | 100 mL | 10 g

- DO NOT freeze.
- Store GAMMAGARD LIQUID ERC in the refrigerator or at room temperature.
- Refrigerated Temperature: 2° to 8°C (36° to 46°F) for up to 36 months.
- Room Temperature: up to 25°C (77°F) for up to 24 months.
- Expiration dates for both storage conditions are printed on the outer carton and vial label.
- Do not use past the applicable expiration date.
- Discard unused portion.

17 PATIENT COUNSELING INFORMATION

Advise the patient to read the FDA-approved patient labeling (Patient Information and Instructions for Use).

Discuss the following with the patient and/or caregivers.

- Hypersensitivity Reactions: Inform patients and/or caregivers that hypersensitivity reactions may occur with GAMMAGARD LIQUID ERC infusion. Prior to starting GAMMAGARD LIQUID ERC ask about a history of allergic reactions to immune globulin or other blood products. Advise patients and/or caregivers to seek immediate medical evaluation if any signs and symptoms of hypersensitivity or acute infusion reactions occur [see Warnings and Precautions (5.1)].
- Renal Injury: Inform patients and/or caregivers that renal injury may occur with GAMMAGARD LIQUID ERC infusion. Advise patients and/or caregivers to seek immediate medical evaluation if any signs and symptoms of renal injury occur such as decreased urine output, sudden weight gain, fluid retention/edema, and/or shortness of breath [see Warnings and Precautions (5.2)].
- Thrombosis: Inform patients and/or caregivers that thrombosis may occur after GAMMAGARD LIQUID ERC infusion. Advise patients and/or caregivers to seek immediate medical evaluation if any signs and symptoms of thrombosis occur such as pain and/or swelling of an arm or leg with warmth over the affected area, discoloration of an arm or leg, unexplained shortness of breath, chest pain or discomfort that worsens on deep breathing, unexplained rapid pulse, numbness or weakness on one side of the body [see Warnings and Precautions (5.4)].
- Aseptic meningitis syndrome (AMS): Inform patients and/or caregivers that AMS may occur after GAMMAGARD LIQUID ERC infusion. Advise patients and/or caregivers to seek immediate medical evaluation if any signs and symptoms of AMS occur such as severe headache, neck stiffness, drowsiness, fever, sensitivity to light, painful eye movements, nausea, and vomiting [see Warnings and Precautions (5.5)].
- Hemolysis: Inform patients and/or caregivers that hemolysis may occur after GAMMAGARD LIQUID ERC infusion. Advise patients and/or caregivers to seek immediate medical evaluation if any signs and symptoms of hemolysis occur such as increased heart rate, fatigue, yellowing of the skin or eyes, and dark-colored urine [see Warnings and Precautions (5.6)].
- Transfusion-Related Acute Lung Injury (TRALI): Inform patients and/or caregivers that TRALI may occur 1 to 6 hours after GAMMAGARD LIQUID ERC infusion. Advise patients and/or caregivers to seek immediate medical evaluation if any signs and symptoms of TRALI occur such as trouble breathing, chest pain, blue lips or extremities, or fever [see Warnings and Precautions (5.7)].
- Transmission of Infectious Agents: Inform patients and/or caregivers that GAMMAGARD LIQUID ERC is made from human plasma and may contain infectious agents that can cause disease (e.g., viruses and, theoretically, the vCJD agent). The risk of GAMMAGARD LIQUID ERC transmitting an infectious agent has been reduced by screening plasma donors for prior exposure, testing donated plasma, and inactivating or removing certain viruses during manufacturing. Patients should report any symptoms that concern them which might be caused by virus infections [see Warnings and Precautions (5.8)].
- Drug Interactions: Inform patients that GAMMAGARD LIQUID ERC can interfere with their immune response to live viral vaccines such as measles, mumps, rubella and varicella, and instruct patients to notify their healthcare professional of this potential interaction when they are receiving vaccinations [see Drug Interactions (7)].

Subcutaneous Administration Only

For self-administration provide clear instructions and training on SC infusion to the patient/caregiver and document the demonstration of their ability to independently administer SC infusions.

- Patients with a history of allergic reactions should not be treated subcutaneously at home until 2 to 3 treatments have been administered and tolerated under medical supervision.
- Ensure the patient understands the importance of consistent weekly SC infusion to maintain appropriate steady IgG levels.
- Instruct the patient to keep a treatment diary/logbook. This diary/logbook should include information about each infusion such as, the time, date, dose, lot number(s) and any reactions.
- Inform the patient that mild to moderate local infusion site reactions (e.g., swelling and redness) are a common side effect of SC treatment, but contact their healthcare professional if a local reaction increases in severity or persists for more than a few days.

Manufactured by:
Takeda Pharmaceuticals U.S.A., Inc.
Cambridge, MA 02142

U.S. License Number: 1898

GAMMAGARD and GAMMAGARD LIQUID are registered trademarks of Baxalta Incorporated.

TAKEDA and are registered trademarks of Takeda Pharmaceutical Company Limited.

©2025 Takeda Pharmaceuticals U.S.A., Inc. All rights reserved.

GLQ 381 R1

PATIENT INFORMATION
GAMMAGARD LIQUID ERC
Immune Globulin Infusion (Human)
10% solution for intravenous or subcutaneous use

What is the most important information I need to know about GAMMAGARD LIQUID ERC?
GAMMAGARD LIQUID ERC can cause the following serious reactions:

- Severe allergic reactions causing difficulty in breathing or skin rashes
- Decreased kidney function or kidney failure
- Blood clots in the heart, brain, lungs or elsewhere in the body
- Severe headache, drowsiness, fever, painful eye movements, or nausea and vomiting
- Dark colored urine, swelling, fatigue, or difficulty breathing

What is GAMMAGARD LIQUID ERC?
GAMMAGARD LIQUID ERC is a single-dose, liquid medicine that contains immunoglobulin G (Human) (IgG) antibodies, which protect the body against infection. GAMMAGARD LIQUID ERC is used to treat the following conditions:
Primary Immunodeficiency Diseases: There are many forms of PI. The most common types of PI result in an inability to make a very important type of protein called antibodies, which help the body fight off infections from bacteria or viruses. GAMMAGARD LIQUID ERC is made from human plasma that is donated by healthy people. GAMMAGARD LIQUID ERC contains antibodies collected from these healthy people that replace the missing antibodies in PI patients.

Who should not use GAMMAGARD LIQUID ERC?
Do not use GAMMAGARD LIQUID ERC if you have a known history of a severe allergic reaction to immune globulin or other blood products. If you have such a history, discuss this with your healthcare provider to determine if GAMMAGARD LIQUID ERC can be given to you.

How should I use GAMMAGARD LIQUID ERC?
GAMMAGARD LIQUID ERC is given into a vein (intravenously) or under the skin (subcutaneously). For patients with PI, infusions into the vein are usually given every 3 or 4 weeks whereas infusions under the skin are given every week. You and your healthcare provider will decide which way is best for you. Most of the time infusions under the skin are given at home by patients or caregivers. Although it is possible to give yourself infusions into the vein at home they are more often given in a hospital or infusion center by a nurse.
Instructions for giving GAMMAGARD LIQUID ERC under the skin (subcutaneously) are provided in the Instructions for Use brochure. Only use GAMMAGARD LIQUID ERC by yourself after you have been instructed by your healthcare provider.

What should I avoid while taking GAMMAGARD LIQUID ERC?
GAMMAGARD LIQUID ERC can make vaccines (like measles/mumps/rubella or chickenpox vaccines) not work as well for you. Before you get any vaccines, tell your healthcare provider that you take GAMMAGARD LIQUID ERC.
Tell your healthcare provider if you are pregnant, or plan to become pregnant, or if you are nursing.

What are the possible or reasonably likely side effects of GAMMAGARD LIQUID ERC?
The following one or more possible reactions may occur at the site of infusion. These generally go away within a few hours and are less likely after the first few infusions.

- Mild or moderate pain
- Swelling
- Itching
- Rash

- Redness
- Bruising
- Warmth
- Bleeding

During the infusion of GAMMAGARD LIQUID ERC, look out for the first signs of the following common side effects:

- Headache
- Migraine
- Fever
- Fatigue
- Itching
- Rash/Hives
- Cough
- Chest pain/tightness
- Pain in extremity
- Diarrhea
- Infusion site leakage
- Joint pain

- Chills/Shaking chills
- Dizziness
- Nausea/Vomiting
- Faster heart rate
- Upper abdominal pain
- Increased blood pressure
- Muscle cramps
- Sore throat
- Heart murmur
- Asthma
- Ear pain
- Mouth ulcer/sore

If any of the following problems occur after starting treatment with GAMMAGARD LIQUID ERC, stop the infusion immediately and contact your healthcare provider or call emergency services. These could be signs of a serious problem.

- Hives, swelling in the mouth or throat, itching, trouble breathing, wheezing, fainting or dizziness. These could be signs of a serious allergic reaction.
- Bad headache with nausea, vomiting, stiff neck, fever, and sensitivity to light. These could be signs of irritation of the lining around your brain.
- Reduced urination, sudden weight gain, or swelling in your legs. These could be signs of a kidney problem.
- Pain, swelling, warmth, redness, or a lump in your legs or arms. These could be signs of blood clots.
- Brown or red urine, fast heart rate, yellow skin or eyes. These could be signs of a liver problem or a blood problem.
- Chest pain or trouble breathing, or blue lips or extremities. These could be signs of a serious heart or lung problem.
- Fever over 100°F. This could be a sign of an infection.

These are not all the possible side effects with GAMMAGARD LIQUID ERC. You can ask your healthcare provider for physician's information leaflet. Tell your healthcare provider about any side effect that bothers you or that do not go away.
Whenever giving yourself treatment at home, you should have another responsible person present to help treat side effects or get help if you have a serious adverse reaction occur. Ask your healthcare provider whether you should have rescue medications, such as antihistamines or epinephrine.
Call your healthcare provider for medical advice about side effects. You may report side effects to FDA at 1-800-FDA-1088.

How do I store GAMMAGARD LIQUID ERC?
Store vials in their original boxes to protect them from light. Do not freeze GAMMAGARD LIQUID ERC.
You can store GAMMAGARD LIQUID ERC in the refrigerator or at room temperature. The maximum storage time for GAMMAGARD LIQUID ERC depends on the storage temperature you choose.
Refrigerator Temperature: at 2° to 8°C (36° to 46°F) for up to 36 months.
Room Temperature: up to 25°C (77°F) for up to 24 months.
The refrigerator and room temperature expiration dates are printed on the vial labels and the box. Always check the expiration date. You should not use the product after the expiration date.
Note: If you remove GAMMAGARD LIQUID ERC from the refrigerator and store it at room temperature, do not refrigerate again.

General information about the safe and effective use of GAMMAGARD LIQUID ERC.
Medicines are sometimes prescribed for purposes other than those listed in a Patient Information leaflet.
Do not use GAMMAGARD LIQUID ERC for a condition for which it was not prescribed. Do not give GAMMAGARD LIQUID ERC to other people, even if they have the same symptoms you have. It may harm them.
This Patient Information leaflet summarizes the most important information about GAMMAGARD LIQUID ERC. If you would like more information, talk to your doctor. You can ask your pharmacist or doctor for information about GAMMAGARD LIQUID ERC that is written for health professionals.

What are the ingredients in GAMMAGARD LIQUID ERC?
Active ingredients: Human normal immunoglobulin 10% solution with less than or equal to 2 µg/mL immunoglobulin A (IgA).
Inactive ingredients: Glycine, Water for Injection, Hydrochloric acid.

Manufactured by:
Takeda Pharmaceuticals U.S.A., Inc.
Cambridge, MA 02142
U.S. License Number: 1898
GAMMAGARD and GAMMAGARD LIQUID are registered trademarks of Baxalta Incorporated.

TAKEDA and are registered trademarks of Takeda Pharmaceutical Company Limited.

©2025 Takeda Pharmaceuticals U.S.A., Inc. All rights reserved.
For more information about GAMMAGARD LIQUID ERC call Takeda Pharmaceuticals U.S.A., Inc. at
1-877-TAKEDA-7 (1-877-825-3327).

This Patient Information has been approved by the U.S. Food and Drug Administration.
Issued: 10/2025
GLQ 381 R1

INSTRUCTIONS FOR USE
GAMMAGARD LIQUID ERC
Immune Globulin Infusion (Human)
10% solution for subcutaneous use

This "Instructions for Use" contains information on how to infuse GAMMAGARD LIQUID ERC

Important Information You Need to Know Before Preparing and Infusing GAMMAGARD LIQUID ERC

Do not use GAMMAGARD LIQUID ERC at home until you get instructions and training from your healthcare professional.

Preparing for your Infusion

Step 1 | Prepare for your Infusion Before you start; - Find a quiet work area with as few distractions as possible. - Clean a work area with an antibacterial cleaner. - Remove GAMMAGARD LIQUID ERC from the refrigerator and take the vial out of the box. - Allow vials to reach room temperature. This may take up to 60 minutes. - Do not apply heat or place it in the microwave. - Do not shake the vial(s).; OR; - Take the vial out of the box, if stored at room temperature. - Do not shake the vial(s).; Repeat this step with as many boxes of GAMMAGARD LIQUID ERC as necessary. Gather your supplies (Figure 1) Collect all the items you will need for the infusion; - Vial(s) of GAMMAGARD LIQUID ERC - Infusion supplies - Infusion pump - Needle sets - Transfer needles - Alcohol swabs - Syringes - Gauze and tape - Sharps container - Treatment logbook | Figure 1
Step 2 | Wash your hands (Figure 2); - Wash your hands thoroughly. - Put on clean gloves if your healthcare provider has instructed you to wear them. | Figure 2
Step 3 | Check the vial and liquid; - Remove the vial from the box. Carefully look at the liquid in the vial of GAMMAGARD LIQUID ERC. - GAMMAGARD LIQUID ERC is a clear, colorless to slightly yellowish liquid. Check for particles or color changes.; - Do not use the vial if: - The liquid looks cloudy, contains particles, or is dark yellow. - The protective flip cap is missing or damaged. - The expiration date on the label has passed.
Step 4 | Vial(s) preparation; - If GAMMAGARD LIQUID ERC is received in a bag or syringe, skip to Step 6. - Remove the protective flip cap from the vial(s). (Figure 3) - Wipe the vial(s) stopper with an alcohol swab and allow to air dry for at least 30 seconds. (Figure 4) | Figure 3 Figure 4
Step 5 | Fill syringe from GAMMAGARD LIQUID ERC vial(s); - Remove sterile syringe from package and attach to a sterile needle. - Pull back on plunger of the syringe to fill it with air, which should equal the amount of liquid you will be taking from the vial. - Insert the needle into the center of the vial stopper. Inject air into the vial and withdraw GAMMAGARD LIQUID ERC into the syringe. (Example: If you withdraw 50 mL of GAMMAGARD LIQUID ERC, inject 50 mL of air into the vial). (Figure 5); If multiple vials are required to achieve the desired dose, repeat this step.; - If using a vented spike: - It is not necessary to inject air into the vial with the syringe. - Attach a sterile syringe to the spike, insert the spike into the center of the stopper, and pull back on the plunger to withdraw the desired volume. | Figure 5
Step 6 | Prepare the infusion pump and tubing; - If you use a syringe driver pump, attach the syringe filled with GAMMAGARD LIQUID ERC to the needle set. On a hard surface, gently push down on the plunger to fill (prime) the pump tubing up to the needle hub. This will ensure that no air is left in the tubing and needle. (Figure 6) - If using a portable pump with GAMMAGARD LIQUID ERC in a bag, follow manufacturer's instructions for preparing the pump and administration tubing, if needed. | Figure 6

Infusing of GAMMAGARD LIQUID ERC

Step 7 | Prepare the infusion site; - Choose an infusion site(s): upper arms, abdomen, thighs, and lower back. (Figure 7, Figure 8) - Make sure the sites are at least 2 inches apart. - Avoid bony areas, visible blood vessels, scars and areas of inflammation (irritation) or infection.; - Select the number of infusion sites based on the volume of the total dose. It is recommended that you not inject more than 20 mL for children and 30 mL for adults into each infusion site. - Rotate sites by choosing opposite sides of the body between future infusions. - Wipe the infusion site(s) with a sterile alcohol wipe beginning at the center of each infusion site and moving outward in a circular motion. - Allow the infusion site(s) to dry (at least 30 seconds). (Figure 9) | Figure 7 Figure 8 Figure 9
Step 8 | Insert the needle (Figure 10); - Remove the needle cover. - Firmly grasp skin and pinch at least one inch of skin between two fingers. - Insert needle with a rapid motion straight into the skin at a 90-degree angle. Tape the needle in place with sterile tape. - Repeat this step for each infusion site. | Figure 10
Step 9 | Check for proper needle placement; - Before starting the infusion, check each needle for correct placement by gently pulling back on the attached syringe plunger and looking for any blood in the needle tubing. (Figure 11) - If you see any blood, remove and throw away the needle into the Sharps container. Repeat filling (priming) and needle insertion steps in a different infusion site with a new needle. | Figure 11
Step 10 | Secure the needle to the skin and start infusion; - Secure the needle(s) in place by putting a sterile clear bandage over the needle. (Figure 12) - Follow the manufacturer's instructions to turn pump on. Check infusion sites occasionally throughout the infusion. | Figure 12
Step 11 | Remove needle set; - After the infusion is complete, remove the needle set by pulling it straight out. Gently press a small piece of gauze over the needle site and cover with a protective dressing. (Figure 13) | Figure 13
Step 12 | Record the infusion; - Remove the peel-off label from GAMMAGARD LIQUID ERC vial, which has the product lot number and expiration date, and place the label in your treatment diary/logbook. Write down the date, time, dose, and any reactions after each infusion.

Storing GAMMAGARD LIQUID ERC

Store vials in their original boxes to protect them from light. Do not freeze GAMMAGARD LIQUID ERC.

You can store GAMMAGARD LIQUID ERC in the refrigerator or at room temperature. The maximum storage time for GAMMAGARD LIQUID ERC depends on the storage temperature you choose.

Refrigerator Temperature: at 2° to 8°C (36° to 46°F) for up to 36 months.

Room Temperature: up to 25°C (77°F) for up to 24 months.

The refrigerator and room temperature expiration dates are printed on the vial labels and the box. Always check the expiration date. You should not use the product after the expiration date.

Note: If you remove GAMMAGARD LIQUID ERC from the refrigerator and store it at room temperature, do not refrigerate again.

Disposing of GAMMAGARD LIQUID ERC

Throw away any unused product in the vial(s) and the disposable supplies into the Sharps container. Dispose of the Sharps container using instructions provided with the container or contact your healthcare provider.

For more information about GAMMAGARD LIQUID ERC, including the current Prescribing Information, call Takeda Pharmaceuticals U.S.A., Inc. at 1-877-TAKEDA-7 (1-877-825-3327).

Manufactured by:
Takeda Pharmaceuticals U.S.A., Inc.
Cambridge, MA 02142

U.S. License Number: 1898

GAMMAGARD and GAMMAGARD LIQUID are registered trademarks of Baxalta Incorporated.

TAKEDA and are registered trademarks of Takeda Pharmaceutical Company Limited.

©2025 Takeda Pharmaceuticals U.S.A., Inc. All rights reserved.

This Instructions for Use document has been approved by the U.S. Food and Drug Administration.

Issued: 10/2025

GLQ 381 R1

PRINCIPAL DISPLAY PANEL - 50 mL Bottle Label

NDC 0944-2705-05 Single-dose vial

Immune Globulin Infusion (Human)

GAMMAGARD LIQUID ERC

10% Solution for Infusion
Less than or equal to 2 µg/mL IgA

5 g
50 mL

For Intravenous or Subcutaneous Administration.
Not made with natural rubber latex.
Refrigeration: 2° to 8°C (36° to 46°F).
Do not freeze.
Room Temperature: up to 25°C (77°F).

Takeda Pharmaceuticals
U.S.A., Inc.
Cambridge, MA 02142
U.S. License No. 1898

Rx Only

LE-07-59902
Takeda

PRINCIPAL DISPLAY PANEL - 50 mL Bottle Carton

NDC 0944-2705-50

Immune Globulin Infusion (Human)

GAMMAGARD LIQUID ERC

10% Solution for Infusion
Less than or equal to 2 µg/mL IgA

5 g
50 mL

For Intravenous or Subcutaneous
Administration

Rx Only

Single-dose vial

Takeda

PRINCIPAL DISPLAY PANEL - 100 mL Bottle Label

NDC 0944-2705-01 Single-dose vial

Immune Globulin Infusion (Human)

GAMMAGARD LIQUID ERC

10% Solution for Infusion
Less than or equal to 2 µg/mL IgA

10 g
100 mL

For Intravenous or Subcutaneous Administration.
Not made with natural rubber latex.
Refrigeration: 2° to 8°C (36° to 46°F).
Do not freeze.
Room Temperature: up to 25°C (77°F).

GTIN: 00309442705017

Takeda Pharmaceuticals
U.S.A., Inc.
Cambridge, MA 02142
U.S. License No. 1898

Rx Only

LE-07-59906
Takeda

PRINCIPAL DISPLAY PANEL - 100 mL Bottle Carton

NDC 0944-2705-10

Immune Globulin Infusion (Human)

GAMMAGARD LIQUID ERC

10% Solution for Infusion
Less than or equal to 2 µg/mL IgA

10 g
100 mL

See enclosed prescribing
information for directions for use.

Stabilized with 0.25M glycine.

No preservative.
Not made with natural rubber latex.

The patient and physician should discuss
the risks and benefits of this product.

Rx Only

Single-dose vial

Takeda